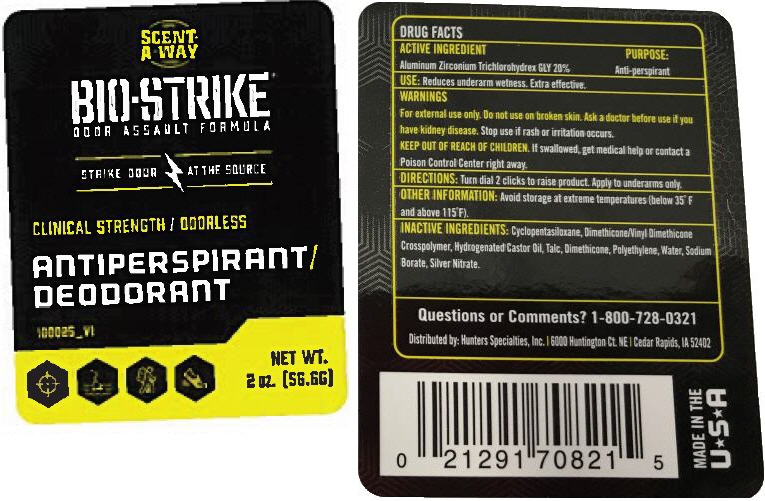 DRUG LABEL: Bio-Strike Antiperspirant/Deodorant
NDC: 63798-821 | Form: STICK
Manufacturer: Hunters Specialties, Inc.
Category: otc | Type: HUMAN OTC DRUG LABEL
Date: 20200108

ACTIVE INGREDIENTS: ALUMINUM ZIRCONIUM TRICHLOROHYDREX GLY 200 mg/1 g
INACTIVE INGREDIENTS: water; HYDROGENATED CASTOR OIL; HIGH DENSITY POLYETHYLENE; Dimethicone; DIMETHICONE/VINYL DIMETHICONE CROSSPOLYMER (SOFT PARTICLE); CYCLOMETHICONE 5; Talc; glycine; Sodium Borate; Silver Nitrate

Bio-Strike® Antiperspirant/Deodorant

Drug Facts

ACTIVE INGREDIENT

Aluminum Zirconium Trichlorohydrex Gly 20%

PURPOSE

Anti-perspirant

Use

Reduces underarm wetness. Extra effective.

WARNINGS

For external use only. Do not use on broken skin. Ask a doctor before use if you have a kidney disease. Stop use if rash or irritation occurs.

KEEP OUT OF REACH OF CHILDREN. If swallowed get medical help or contact a Poison Control Center right away.

DIRECTIONS

Turn dial 2 clicks to raise product. Apply to underarms only.

OTHER INFORMATION

Avoid storage at extreme temperatures (below 35˚F and above 115˚F).

INACTIVE INGREDIENTS

Cyclopentasiloxane, Dimethicone/Vinyl Dimethicone Crosspolymer, Hydrogenated Castor Oil, Talc, Dimethicone, Polyethylene, Water, Sodium Borate, Silver Nitrate.

Questions or Comments?

1-800-728-0321

Distributed by Hunters Specialties, Inc.[6000 Huntington Ct, NE]Cedar Rapids , IA 52402

PRINCIPAL DISPLAY PANEL - 56.6 G Canister Label

ODOR
SCENT-
A-WAY®
CONTROL

BIO-STRIKE®
ODOR ASSAULT FORMULA

STRIKE ODOR AT THE SOURCE

CLINICAL STRENGTH / ODORLESS

ANTIPERSPIRANT/
DEODORANT

100025_V1

NET WT.
2 oz. [56.6G]